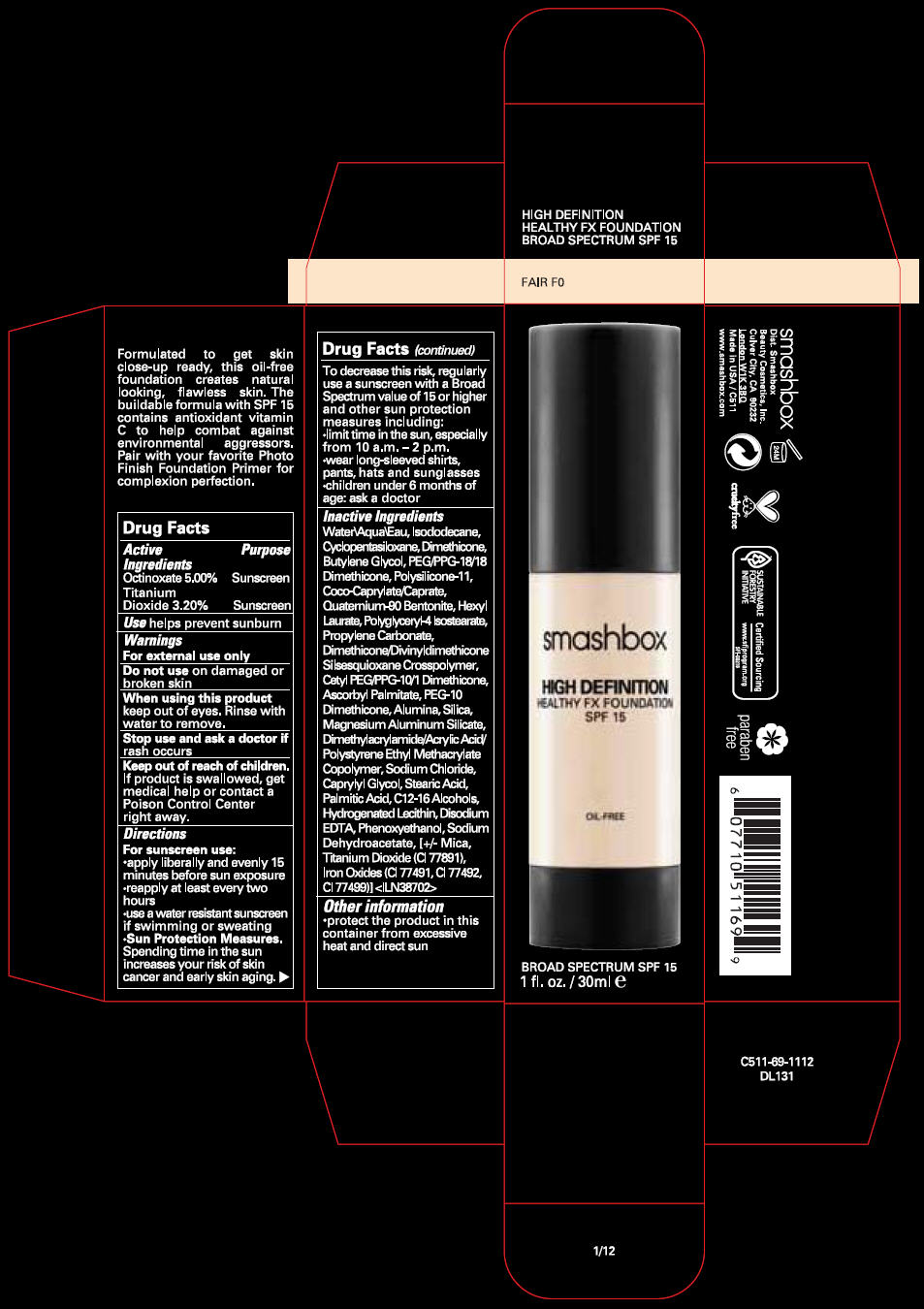 DRUG LABEL: SMASHBOX 
NDC: 10348-005 | Form: LIQUID
Manufacturer: SMASHBOX  BEAUTY COSMETICS, INC
Category: otc | Type: HUMAN OTC DRUG LABEL
Date: 20120327

ACTIVE INGREDIENTS: OCTINOXATE 5 mL/100 mL; TITANIUM DIOXIDE 3.2 mL/100 mL
INACTIVE INGREDIENTS: WATER; ISODODECANE; CYCLOMETHICONE 5; DIMETHICONE; BUTYLENE GLYCOL; PEG/PPG-18/18 DIMETHICONE; HEXYL LAURATE; POLYGLYCERYL-4 ISOSTEARATE; PROPYLENE CARBONATE; ASCORBYL PALMITATE; ALUMINUM OXIDE; SILICON DIOXIDE; MAGNESIUM ALUMINUM SILICATE; SODIUM CHLORIDE; CAPRYLYL GLYCOL; STEARIC ACID; PALMITIC ACID; C12-16 ALCOHOLS; EDETATE DISODIUM; PHENOXYETHANOL; SODIUM DEHYDROACETATE; MICA; FERRIC OXIDE RED; FERRIC OXIDE YELLOW; FERROSOFERRIC OXIDE

SMASHBOX
HIGH DEFINITION HEALTHY FX FOUNDATION SPF 15

Drug Facts

ACTIVE INGREDIENT

Active Ingredients | Purpose
Octinoxate 5.00% | Sunscreen
Titanium Dioxide 3.20% | Sunscreen

Use

helps prevent sunburn

Warnings

For external use only

Do not use on damaged or broken skin

When using this product keep out of eyes. Rinse with water to remove.

Stop use and ask a doctor if rash occurs

Keep out of reach of children. If product is swallowed, get medical help or contact a Poison Control Center right away.

Directions

For sunscreen use:

- apply liberally and evenly 15 minutes before sun exposure
- reapply at least every two hours
- use a water resistant sunscreen if swimming or sweating
- Sun Protection Measures. Spending time in the sun increases your risk of skin cancer and early skin aging. To decrease this risk, regularly use a sunscreen with a Broad Spectrum value of 15 or higher and other sun protection measures including:
  - limit time in the sun, especially from 10 a.m. – 2 p.m.
  - wear long-sleeved shirts, pants, hats and sunglasses
  - children under 6 months of age: ask a doctor

Inactive Ingredients

Water\Aqua\Eau, Isododecane, Cyclopentasiloxane, Dimethicone, Butylene Glycol, PEG/PPG-18/18 Dimethicone, Polysilicone-11, Coco-Caprylate/Caprate, Quaternium-90 Bentonite, Hexyl Laurate, Polyglyceryl-4 Isostearate, Propylene Carbonate, Dimethicone/Divinyldimethicone Silsesquioxane Crosspolymer, Cetyl PEG/PPG-10/1 Dimethicone, Ascorbyl Palmitate, PEG-10 Dimethicone, Alumina, Silica, Magnesium Aluminum Silicate, Dimethylacrylamide/Acrylic Acid/Polystyrene Ethyl Methacrylate Copolymer, Sodium Chloride, Caprylyl Glycol, Stearic Acid, Palmitic Acid, C12-16 Alcohols, Hydrogenated Lecithin, Disodium EDTA, Phenoxyethanol, Sodium Dehydroacetate, [+/- Mica, Titanium Dioxide (CI 77891), Iron Oxides (CI 77491, CI 77492, CI 77499)] <ILN38702>

Other information

- protect the product in this container from excessive heat and direct sun

Dist. Smashbox
Beauty Cosmetics, Inc.
Culver City, CA 90232

PRINCIPAL DISPLAY PANEL - 30ml Cylinder Carton

smashbox

HIGH DEFINITION
HEALTHY FX FOUNDATION
SPF 15

OIL-FREE

BROAD SPECTRUM SPF 15
1 fl. oz. / 30ml e